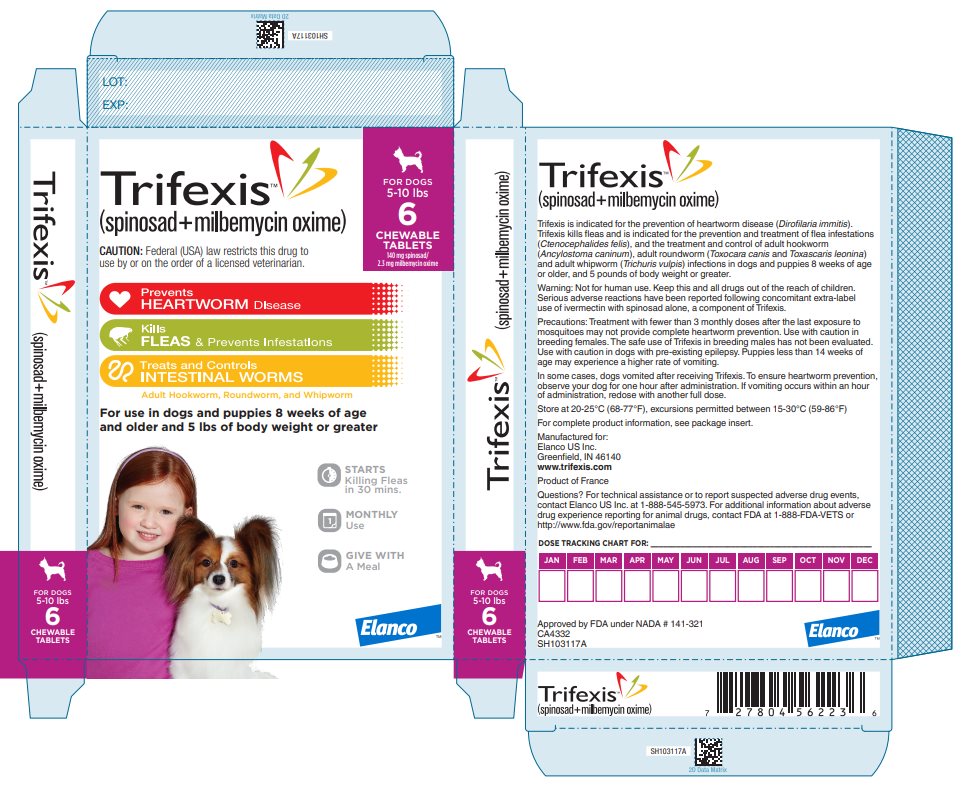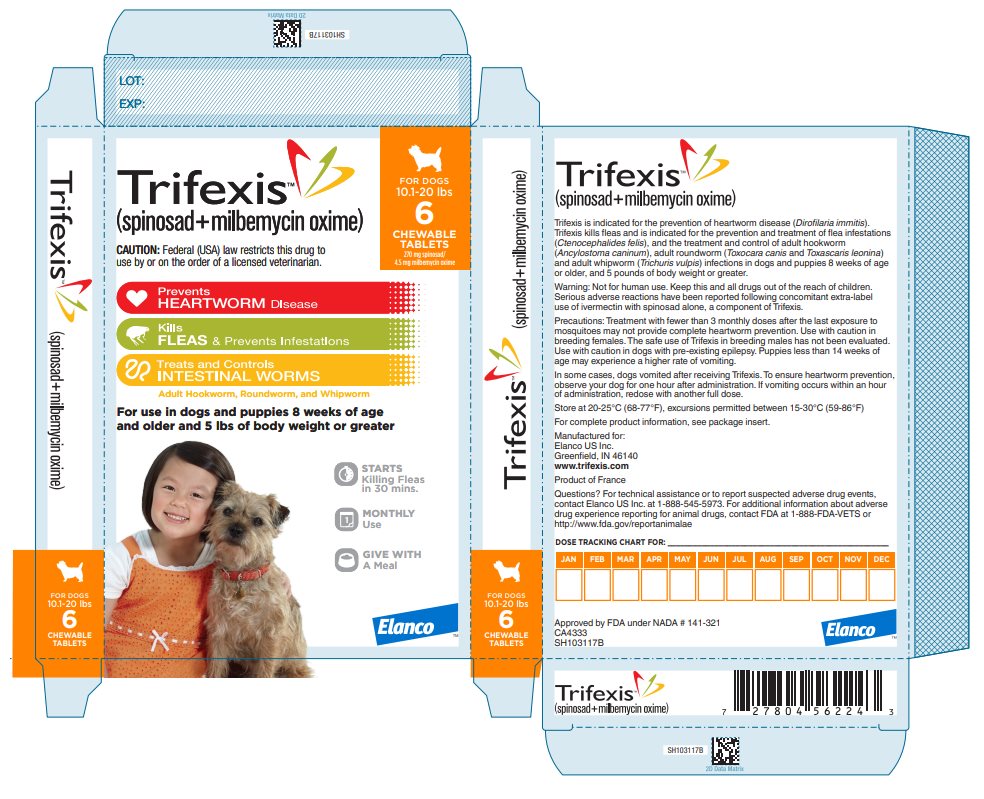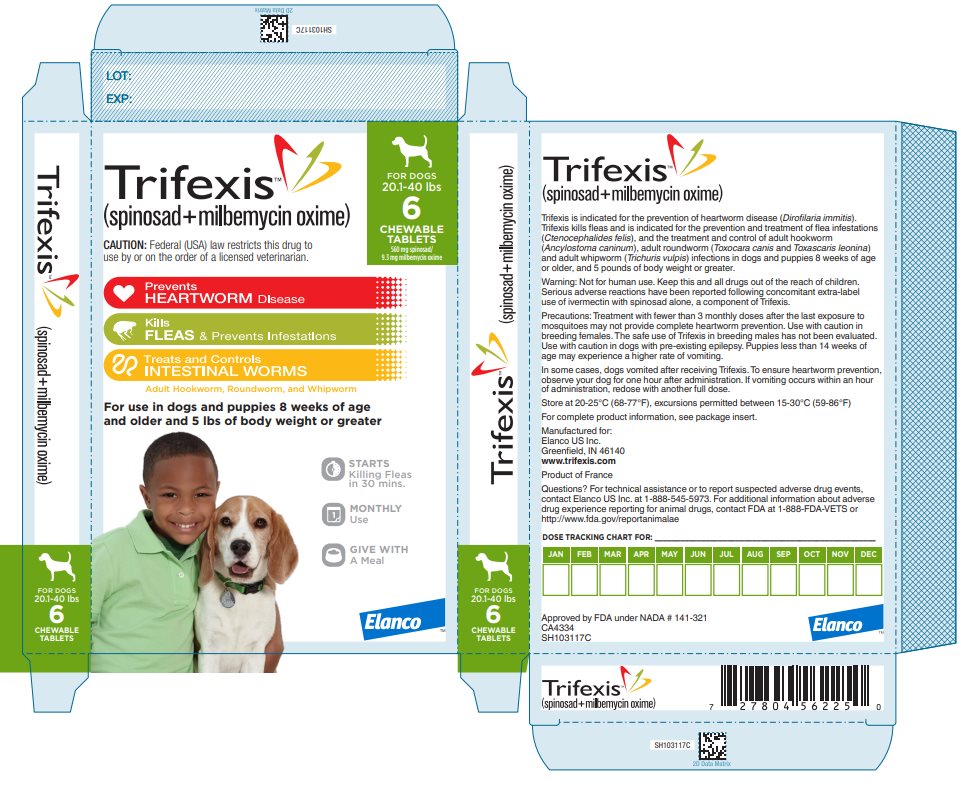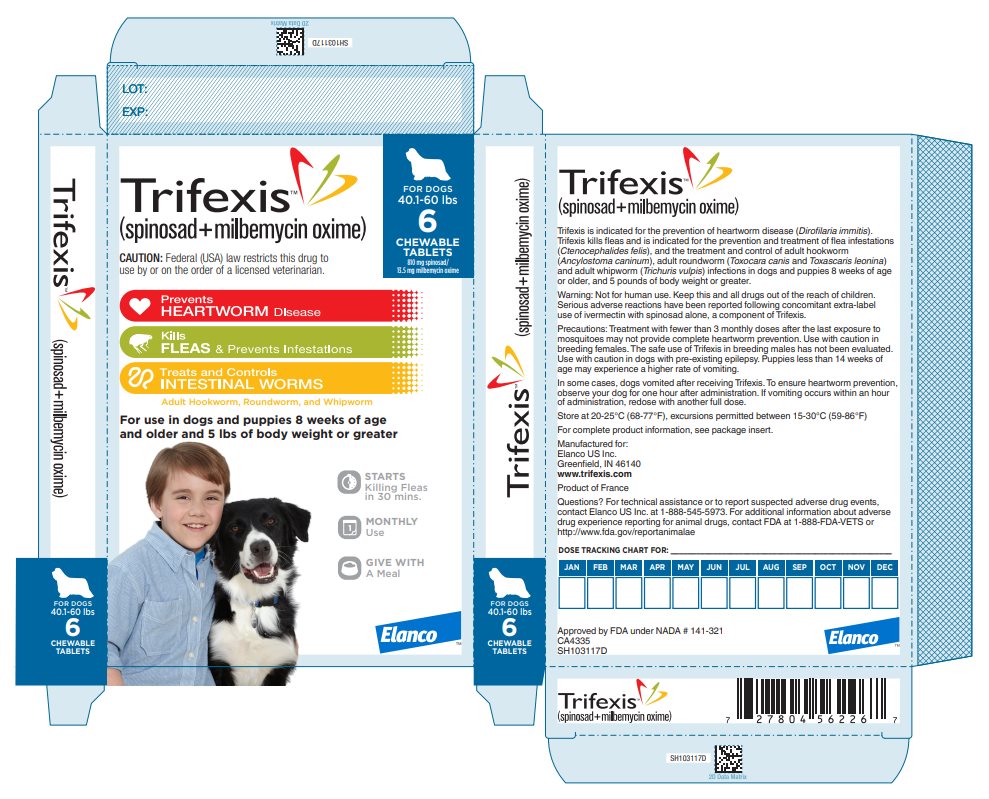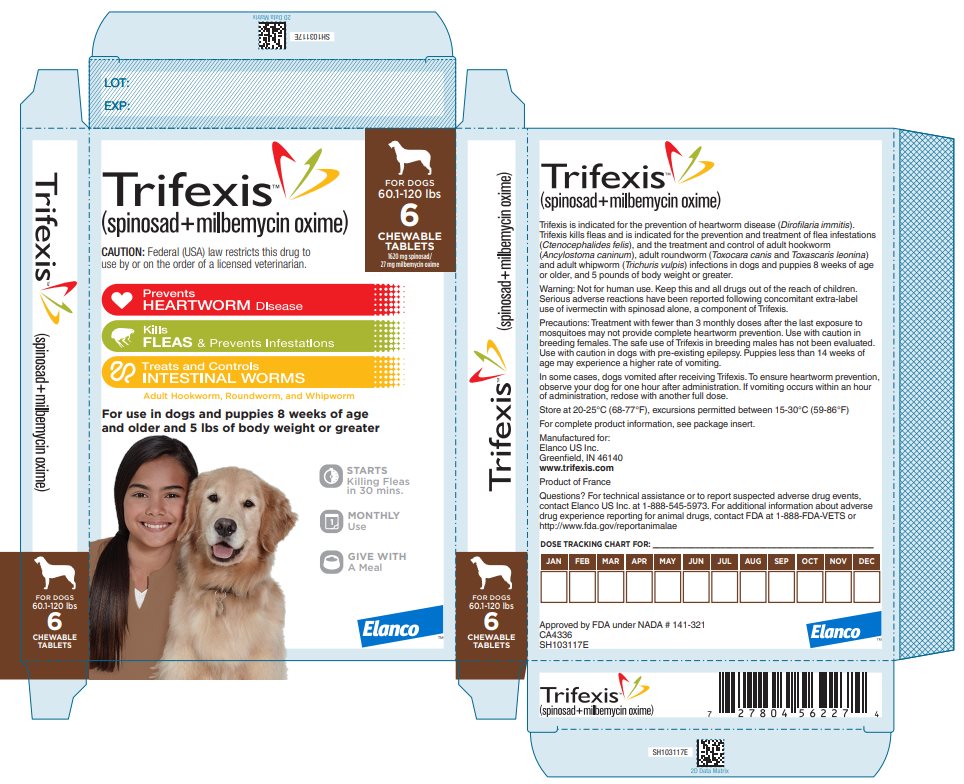 DRUG LABEL: Trifexis
NDC: 58198-0042 | Form: TABLET
Manufacturer: Elanco US Inc.
Category: animal | Type: PRESCRIPTION ANIMAL DRUG LABEL
Date: 20260105

ACTIVE INGREDIENTS: spinosad 140 mg/1 1; milbemycin oxime 2.3 mg/1 1

TRIFEXIS™

(spinosad + milbemycin oxime)

Chewable Tablets

Caution: Federal (USA) law restricts this drug to use by or on the order of a licensed veterinarian.

Description:

TRIFEXIS (spinosad and milbemycin oxime) is available in five sizes for oral administration to dogs and puppies according to their weight. Each chewable flavored tablet is formulated to provide a minimum spinosad dose of 13.5 mg/lb (30 mg/kg) and a minimum milbemycin oxime dose of 0.2 mg/lb (0.5 mg/kg). Spinosad is a member of the spinosyns class of insecticides, which are non-antibacterial tetracyclic macrolides. Spinosad contains two major factors, spinosyn A and spinosyn D, derived from the naturally occurring bacterium, Saccharopolyspora spinosa. Spinosyn A and spinosyn D have the chemical compositions C41H65NO10 and C42H67NO10, respectively. Milbemycin oxime is a macrocyclic lactone anthelmintic, containing two major factors, A3 and A4 of milbemycin oxime. The approximate ratio of A3:A4 is 20:80. Milbemycin A4 5-oxime has the chemical composition of C32H45NO7 and milbemycin A3 5-oxime has the chemical composition of C31H43NO7.

Indications:

TRIFEXIS is indicated for the prevention of heartworm disease (Dirofilaria immitis).

TRIFEXIS kills fleas and is indicated for the prevention and treatment of flea infestations (Ctenocephalides felis), and the treatment and control of adult hookworm (Ancylostoma caninum), adult roundworm (Toxocara canis and Toxascaris leonina) and adult whipworm (Trichuris vulpis) infections in dogs and puppies 8 weeks of age or older and 5 pounds of body weight or greater.

Dosage and Administration:

TRIFEXIS is given orally, once a month at the minimum dosage of 13.5 mg/lb (30 mg/kg) spinosad and 0.2 mg/lb (0.5 mg/kg) milbemycin oxime body weight. For heartworm prevention, give once monthly for at least 3 months after exposure to mosquitoes (see EFFECTIVENESS).

Dosage Schedule:

Body Weight | Spinosad Per Tablet (mg) | Milbemycin oxime Per Tablet (mg) | Tablets Administered
5 to 10 lbs | 140 | 2.3 | One
10.1 to 20 lbs | 270 | 4.5 | One
20.1 to 40 lbs | 560 | 9.3 | One
40.1 to 60 lbs | 810 | 13.5 | One
60.1 to 120 lbs | 1620 | 27 | One
Over 120 lbs | Administer the appropriate combination of tablets

Administer TRIFEXIS with food for maximum effectiveness. To ensure heartworm prevention, owners should observe the dog for one hour after dosing. If vomiting occurs within an hour of administration, redose with another full dose. If a dose is missed and a monthly interval between doses is exceeded, then immediate administration of TRIFEXIS with food and resumption of monthly dosing will minimize the opportunity for the development of adult heartworm infections and flea reinfestations.

Heartworm Prevention:

TRIFEXIS should be administered at monthly intervals beginning within 1 month of the dog's first seasonal exposure and continuing until at least 3 months after the dog's last seasonal exposure to mosquitoes (see EFFECTIVENESS). TRIFEXIS may be administered year round without interruption. When replacing another heartworm preventative product, the first dose of TRIFEXIS should be given within a month of the last dose of the former medication.

Flea Treatment and Prevention:

Treatment with TRIFEXIS may begin at any time of the year, preferably starting one month before fleas become active and continuing monthly through the end of flea season. In areas where fleas are common year-round, monthly treatment with TRIFEXIS should continue the entire year without interruption.

To minimize the likelihood of flea reinfestation, it is important to treat all animals within a household with an approved flea protection product.

Intestinal Nematode Treatment and Control:

TRIFEXIS also provides treatment and control of roundworms (T. canis, T. leonina), hookworms (A. caninum) and whipworms (T. vulpis). Dogs may be exposed to and can become infected with roundworms, whipworms and hookworms throughout the year, regardless of season or climate. Clients should be advised of measures to be taken to prevent reinfection with intestinal parasites.

Contraindications:

There are no known contraindications to the use of TRIFEXIS.

Warnings:

Not for human use. Keep this and all drugs out of the reach of children.

Serious adverse reactions have been reported following concomitant extra-label use of ivermectin with spinosad alone, a component of TRIFEXIS (see ADVERSE REACTIONS).

Precautions:

Treatment with fewer than 3 monthly doses after the last exposure to mosquitoes may not provide complete heartworm prevention (see EFFECTIVENESS).

Prior to administration of TRIFEXIS, dogs should be tested for existing heartworm infection. At the discretion of the veterinarian, infected dogs should be treated with an adulticide to remove adult heartworms. TRIFEXIS is not effective against adult D. immitis. While the number of circulating microfilariae may decrease following treatment, TRIFEXIS is not indicated for microfilariae clearance (see ANIMAL SAFETY).

Mild, transient hypersensitivity reactions manifested as labored respiration, vomiting, salivation and lethargy, have been noted in some dogs treated with milbemycin oxime carrying a high number of circulating microfilariae. These reactions are presumably caused by release of protein from dead or dying microfilariae.

Use with caution in breeding females (see ANIMAL SAFETY). The safe use of TRIFEXIS in breeding males has not been evaluated.

Use with caution in dogs with pre-existing epilepsy (see ADVERSE REACTIONS).

Puppies less than 14 weeks of age may experience a higher rate of vomiting (see ANIMAL SAFETY).

Adverse Reactions:

In a well-controlled US field study, which included a total of 352 dogs (176 treated with TRIFEXIS and 176 treated with an active control), no serious adverse reactions were attributed to administration of TRIFEXIS. All reactions were regarded as mild.

Over the 180-day study period, all observations of potential adverse reactions were recorded. Reactions that occurred at an incidence >1% (average monthly rate) within any of the 6 months of observation are presented in the following table. The most frequently reported adverse reaction in dogs in the TRIFEXIS group was vomiting.

Average Monthly Rate (%) of Dogs With Adverse Reactions

Adverse Reaction | TRIFEXIS Chewable Tabletsa | Active Control Tabletsa
Vomiting | 6.13 | 3.08
Pruritus | 4.00 | 4.91
Lethargy | 2.63 | 1.54
Diarrhea | 2.25 | 1.54
Dermatitis | 1.47 | 1.45
Skin Reddening | 1.37 | 1.26
Decreased appetite | 1.27 | 1.35
Pinnal Reddening | 1.18 | 0.87
an=176 dogs

In the US field study, one dog administered TRIFEXIS experienced a single mild seizure 2 ½ hours after receiving the second monthly dose. The dog remained enrolled and received four additional monthly doses after the event and completed the study without further incident.

Following concomitant extra-label use of ivermectin with spinosad alone, a component of TRIFEXIS, some dogs have experienced the following clinical signs: trembling/twitching, salivation/drooling, seizures, ataxia, mydriasis, blindness and disorientation. Spinosad alone has been shown to be safe when administered concurrently with heartworm preventatives at label directions.

In US and European field studies, no dogs experienced seizures when dosed with spinosad alone at the therapeutic dose range of 13.5-27.3 mg/lb (30-60 mg/kg), including 4 dogs with pre-existing epilepsy. Four epileptic dogs that received higher than the maximum recommended dose of 27.3 mg/lb (60 mg/kg) experienced at least one seizure within the week following the second dose of spinosad, but no seizures following the first and third doses. The cause of the seizures observed in the field studies could not be determined.

For technical assistance or to report suspected adverse drug events, contact Elanco US Inc. at 1-888-545-5973. For additional information about adverse drug experience reporting for animal drugs, contact FDA at 1-888-FDA-VETS or http://www.fda.gov/reportanimalae

Post Approval Experience (Mar 2012):

The following adverse reactions are based on post-approval adverse drug event reporting. The adverse reactions are listed in decreasing order of frequency: vomiting, depression/lethargy, pruritus, anorexia, diarrhea, trembling/shaking, ataxia, seizures, hypersalivation, and skin reddening.

Mode of Action:

The primary target of action of spinosad, a component of TRIFEXIS, is an activation of nicotinic acetylcholine receptors (nAChRs) in insects. Spinosad does not interact with known insecticidal binding sites of other nicotinic or GABAergic insecticides such as neonicotinoids, fiproles, milbemycins, avermectins and cyclodienes. Insects treated with spinosad show involuntary muscle contractions and tremors resulting from activation of motor neurons. Prolonged spinosad-induced hyperexcitation results in prostration, paralysis and flea death. The selective toxicity of spinosad between insects and vertebrates may be conferred by the differential sensitivity of the insect versus vertebrate nAChRs.

Milbemycin oxime, a component of TRIFEXIS, acts by binding to glutamate-gated chloride ion channels in invertebrate nerve and muscle cells. Increased permeability by the cell membrane to chloride ions causes hyperpolarization of affected cells and subsequent paralysis and death of the intended parasites. Milbemycin oxime may also act by disrupting the transmission of invertebrate neurotransmitters, notably gamma amino butyric acid (GABA).

Effectiveness:

Heartworm Prevention:

In a well-controlled laboratory study, TRIFEXIS was 100% effective against induced heartworm infections when administered for 3 consecutive monthly doses.

Two consecutive monthly doses did not provide 100% effectiveness against heartworm infection. In another well-controlled laboratory study, a single dose of TRIFEXIS was 100% effective against induced heartworm infections.

In a well-controlled six-month US field study conducted with TRIFEXIS, no dogs were positive for heartworm infection as determined by heartworm antigen testing performed at the end of the study and again three months later.

Flea Treatment and Prevention:

In a well-controlled laboratory study, TRIFEXIS demonstrated 100% effectiveness on the first day following treatment and 100% effectiveness on Day 30. In a well-controlled laboratory study, spinosad, a component of TRIFEXIS, began to kill fleas 30 minutes after administration and demonstrated 100% effectiveness within 4 hours. Spinosad, a component of TRIFEXIS, kills fleas before they can lay eggs. If a severe environmental infestation exists, fleas may persist for a period of time after dose administration due to the emergence of adult fleas from pupae already in the environment. In field studies conducted in households with existing flea infestations of varying severity, flea reductions of 98.0% to 99.8% were observed over the course of 3 monthly treatments with spinosad alone. Dogs with signs of flea allergy dermatitis showed improvement in erythema, papules, scaling, alopecia, dermatitis/pyodermatitis and pruritus as a direct result of eliminating the fleas.

Treatment and Control of Intestinal Nematode Infections:

In well-controlled laboratory studies, TRIFEXIS was ≥ 90% effective in removing naturally and experimentally induced adult roundworm, whipworm and hookworm infections.

Palatability:

TRIFEXIS is a flavored chewable tablet. In a field study of client-owned dogs where 175 dogs were each offered TRIFEXIS once a month for 6 months, dogs voluntarily consumed 54% of the doses when offered plain as if a treat, and 33% of the doses when offered in or on food. The remaining 13% of doses were administered like other tablet medications.

Animal Safety:

TRIFEXIS was tested in pure and mixed breeds of healthy dogs in well-controlled clinical and laboratory studies. No dogs were withdrawn from the field studies due to treatment- related adverse reactions.

In a margin of safety study, TRIFEXIS was administered orally to 8-week-old Beagle puppies at doses of 1, 3, and 5 times the upper half of the therapeutic dose band, every 28 days for 6 dosing periods. Vomiting was seen in all groups including control animals with similar frequency. Adverse reactions seen during the course of the study were salivation, tremors, decreased activity, coughing and vocalization.

Body weights were similar between control and treated groups throughout the study. Treatment with TRIFEXIS was not associated with any clinically significant hematology, clinical chemistry or gross necropsy changes. One 5X dog had minimal glomerular lipidosis observed microscopically. The clinical relevance of this finding is unknown.

Plasma spinosyn A, spinosyn D, milbemycin A3 5-oxime and milbemycin A4 5-oxime concentrations increased throughout the study. At each dosing period, plasma spinosyn A and spinosyn D concentrations were greater than proportional across the dose range 1 to 5X. Plasma milbemycin A4 5-oxime concentrations appeared to be dose proportional across range 1 to 5X by the end of the study. Plasma concentrations of spinosad and milbemycin oxime indicate that expected systemic exposures were achieved throughout the study.

In an avermectin-sensitive Collie dog study, TRIFEXIS was administered orally at 1, 3, and 5 times the upper half of the recommended therapeutic dose band every 28 days. No signs of avermectin sensitivity were observed after administration of TRIFEXIS during the study period to avermectin-sensitive Collie dogs. The adverse reactions observed in the treatment groups were vomiting and diarrhea. Body weights in all treatment groups were comparable to the control group. Hematology and clinical chemistry parameters showed no clinically significant changes from study start to end, and all dogs were considered healthy throughout the study.

In a heartworm positive safety study, TRIFEXIS was administered orally at 1, 3, and 5 times the upper half of the therapeutic dose band to Beagle dogs with adult heartworm infections and circulating microfilariae, every 28 days for 3 treatments. Vomiting was observed in one dog in the 1X group, in three dogs in the 3X group, and in one dog in the 5X group. All but one incident of vomiting was observed on the treatment day during the first treatment cycle. The vomiting was mild and self-limiting. Hypersensitivity reactions were not observed in any of the treatment groups. Microfilariae counts decreased with treatment.

In a reproductive safety study, TRIFEXIS was administered orally to female dogs at 1 and 3 times the upper half of the therapeutic dose band every 28 days prior to mating, during gestation and during a six-week lactation period. Dogs with confirmed fetal heartbeats on ultrasound examination were evaluated for reproductive safety. One 3X and one 1X group female did not become pregnant. No treatment-related adverse reactions or signs of avermectin toxicosis were noted for adult females. Adult females in the 3X group lost weight during the 6-week pre-mating period, while control group females gained weight during that time. The body weights of the treated groups were comparable to the control group during gestation and post-parturition phases of the study. Gestation length, litter average body weight, litter size, stillborn pups, pup survival and the proportion of pups with malformations were comparable between treated and control dam groups. Malformations in the 1X group included a pup with cleft palate and a littermate with anophthalmia, fused single nares, misshapen palate, hydrocephalus, omphalocele and malpositioned testes; a pup with a malformation of the anterior tip of the urinary bladder and umbilical blood vessel; and a pup with patent ductus arteriosus (PDA). Malformations in the 3X group included three littermates with PDA. Malformations in the control group included a pup with a malformed sternum and a pup with PDA and a malpositioned superior vena cava. Clinical findings in pups of the treated groups were comparable to the control group except for one 1X group pup that was smaller and less coordinated than its littermates and had tremors when excited. The relationship between spinosad and milbemycin oxime treatment and the 1X and 3X dogs that did not become pregnant, the specific pup malformations and the unthrifty 1X group pup are unknown. The incidence of cleft palate is not unexpected based on the historical data collected at the breeding site.

In a margin of safety study with spinosad alone, 6-week old Beagle puppies were administered average doses of 1.5, 4.4, and 7.4 times the maximum recommended dose at 28-day intervals over a 6-month period. Vomiting was observed across all treatments, including controls, and was observed at an increased rate at elevated doses. Vomiting most often occurred 1 hour following administration and decreased over time and stabilized when puppies reached 14 weeks of age.

Storage Information:

Store at 20-25°C (68-77°F), excursions permitted between 15-30°C (59-86°F).

How Supplied:

TRIFEXIS is available in five tablet sizes. Each tablet size is available in color-coded packages of 6 tablets.

5-10 lbs (140 mg spinosad and 2.3 mg milbemycin oxime)

10.1-20 lbs (270 mg spinosad and 4.5 mg milbemycin oxime)

20.1-40 lbs (560 mg spinosad and 9.3 mg milbemycin oxime)

40.1-60 lbs (810 mg spinosad and 13.5 mg milbemycin oxime)

60.1-120 lbs (1620 mg spinosad and 27 mg milbemycin oxime)

Approved by FDA under NADA # 141-321

Manufactured for:
Elanco US Inc.
Greenfield, IN 46140

www.trifexis.com

Trifexis, Elanco and the diagonal bar logo are trademarks of Elanco or its affiliates.

CA4332

CA4333

CA4334

CA4335

CA4336

Revised: July 2024

Elanco™

Information for Dog Owners

Your veterinarian has chosen to prescribe TRIFEXIS Chewable Tablets for the prevention of heartworm disease (Dirofilaria immitis), to kill fleas and for the prevention and treatment of flea infestations (Ctenocephalides felis), and the treatment and control of adult hookworm (Ancylostoma caninum), adult roundworm (Toxocara canis and Toxascaris leonina) and adult whipworm (Trichuris vulpis) infections in dogs and puppies 8 weeks of age or older and 5 pounds of body weight or greater. Controlling these parasites is very important to the health of your dog. Please read this leaflet, which describes the proper use of TRIFEXIS. If you have any questions about this information, please consult your veterinarian. Additional information can be found at www.trifexis.com.

What is TRIFEXIS?

TRIFEXIS is a chewable, flavored tablet that you give orally to your dog once-a-month to kill fleas, to prevent flea infestations, to treat and control hookworms, whipworms and roundworms, and to prevent heartworm disease. TRIFEXIS is for monthly use in dogs and puppies 8 weeks of age or older and 5 pounds of body weight or greater. If you do not administer TRIFEXIS monthly throughout the year, the final dose must be given no fewer than three months following the last exposure to mosquitoes.

Why has my veterinarian prescribed TRIFEXIS?

Your veterinarian has prescribed TRIFEXIS as a way of preventing your dog from developing problems caused by infection with three commonly occurring parasite categories. Heartworm infection can make dogs very sick and can even be fatal. This parasite is spread to dogs by mosquitoes. TRIFEXIS can prevent flea infestations from becoming established, and can also remove any fleas that are on your dog at the time of treatment. TRIFEXIS will also treat and control common adult intestinal worm infections (roundworms, hookworms and whipworms).

Should I give TRIFEXIS each month all year round?

Consult your veterinarian regarding the need for year round use of TRIFEXIS. If you do not administer TRIFEXIS monthly throughout the year, the final dose must be given no fewer than three months following the last exposure to mosquitoes.

Will TRIFEXIS kill heartworms?

TRIFEXIS prevents heartworm disease by killing certain stages that develop after an infected mosquito bites a dog. As with other heartworm preventatives, TRIFEXIS does not kill adult heartworms. Speak to your veterinarian about treatment options if your dog is diagnosed with an adult heartworm infection.

Will my dog still need to be tested for heartworm infection while taking TRIFEXIS?

You should speak to your veterinarian about the frequency of heartworm testing while your dog is taking TRIFEXIS.

How do I switch to TRIFEXIS from another heartworm preventative?

Follow the advice of your veterinarian about switching heartworm preventatives.

What should I discuss with my veterinarian regarding TRIFEXIS for my dog?

Your veterinarian is your dog's healthcare expert and can make the best recommendation for medications for your dog. This includes the prevention, control and/or treatment of parasites such as fleas, heartworms and intestinal parasites that may cause conditions that include flea allergy dermatitis, anemia and heart disease. Key points of your discussion may include the following:

- As with other heartworm preventatives, dogs should be tested for heartworm prior to beginning treatment with TRIFEXIS.
- If a dose is missed and a monthly interval between doses is exceeded, then immediately give TRIFEXIS with food and resume monthly dosing. This practice will minimize the opportunity for heartworms to grow. Also, continuing normal monthly dosing will allow you to gain control of any flea or intestinal parasites that might have infected your dog.
- To minimize the likelihood of fleas continuing to jump onto your dog, it is important to treat all household pets with an approved flea protection product.
- TRIFEXIS is not for use in humans. Like all medications, keep TRIFEXIS out of reach of children.

How should I give TRIFEXIS to my dog?

Give TRIFEXIS with food for maximum effectiveness. TRIFEXIS is a chewable tablet and may be offered as a treat. Consult your veterinarian regarding the need for year round administration of TRIFEXIS.

What if I give more than the prescribed amount of TRIFEXIS to my dog?

Contact your veterinarian as soon as possible if you believe your dog has ingested more than the recommended dose of TRIFEXIS. In a study in which dogs were dosed at 1, 3, and 5 times the upper half of the recommended dose, dogs exhibited vomiting, tremors, decreased activity, salivation, coughing and vocalization.

Should I restrict either my dog's activity or contact with my dog after the tablet is consumed?

Since TRIFEXIS is an oral formulation, you may maintain normal activities and interactions with your dog.

How quickly will TRIFEXIS kill fleas?

In a laboratory study of spinosad alone, an active ingredient of TRIFEXIS, spinosad started to kill fleas within 30 minutes and killed 100% of the fleas within 4 hours. TRIFEXIS kills fleas before they can lay eggs.

Does seeing fleas on my dog mean that the treatment is not working?

TRIFEXIS kills fleas before they can lay eggs when used monthly according to the label directions. Remember that all animals in the household should be treated with an approved flea product to help control the flea population.

Your dog can continue to be exposed to the fleas that live in the environment. When fleas jump onto your dog, they will be killed by TRIFEXIS.

If within a month after your dog receives TRIFEXIS you see fleas on your dog, it is most likely that these are new fleas. These new fleas will be killed before they can produce eggs that contaminate the environment. Continued monthly use of TRIFEXIS can prevent any new infestations.

What if I see worms in my dog's stool during the month after administration of TRIFEXIS?

TRIFEXIS is indicated to treat and control intestinal parasite infections of adult hookworms, roundworms and whipworms. In occasional cases, it is possible that the action of TRIFEXIS in killing the intestinal worms will lead to the dog expelling them in the stool. If you have questions, consult with your veterinarian for measures you can take to prevent a reinfection with intestinal parasites.

Is it safe to give my dog TRIFEXIS?

TRIFEXIS has been demonstrated to be safe in pure and mixed breeds of healthy dogs when used according to label directions for dogs and puppies 8 weeks of age and older and five pounds of body weight or greater. You should discuss the use of TRIFEXIS with your veterinarian prior to use if your dog has a history of epilepsy (seizures). Puppies less than 14 weeks of age may experience a higher rate of vomiting.

Is it safe to give my breeding dogs TRIFEXIS?

Ask your veterinarian about the use of TRIFEXIS prior to use in breeding females. The safe use of TRIFEXIS in male dogs intended for breeding has not been evaluated.

What side effects might occur with TRIFEXIS?

Like all medications, sometimes side effects may occur. In some cases, dogs vomited after receiving TRIFEXIS. To ensure heartworm prevention, observe your dog for one hour after administration. If vomiting occurs within an hour of administration, redose with another full dose.

During field studies, no severe or prolonged vomiting occurred.

Additional adverse reactions observed in the clinical studies were itching, decreased activity, diarrhea, inflammation of the skin, redness of the skin, decreased appetite and redness of the ear. All reactions were regarded as mild.

Since the introduction of TRIFEXIS, additional side effects reported are trembling/shaking, ataxia, seizures and hypersalivation.

For technical assistance or to report suspected adverse drug events, contact Elanco US Inc. at 1-888-545-5973. For additional information about adverse drug experience reporting for animal drugs, contact FDA at 1-888-FDA-VETS or http://www.fda.gov/reportanimalae

Can other medications be given while my dog is taking TRIFEXIS?

Yes, TRIFEXIS has been given safely with a wide variety of products and medications. Your veterinarian should be made aware of all products that you administered and/or intend to administer to your dog.

How should TRIFEXIS be stored?

Store at 68-77°F (20-25°C). Temporary periods of time outside this range between 59-86°F (15 -30°C) are permitted.

www.trifexis.com

Trifexis, Elanco and the diagonal bar logo are trademarks of Elanco or its affiliates.

© 2024 Elanco or its affiliates

PA104092X

Elanco™

Principal Display Panel - Trifexis 140 mg Carton Label

Trifexis™

(spinosad + milbemycin oxime)

FOR DOGS
5-10 lbs

6
CHEWABLE
TABLETS

140 mg spinosad/
2.3 mg milbemycin oxime

CAUTION: Federal (USA) law restricts this drug to
use by or on the order of a licensed veterinarian.

Prevents
HEARTWORM Disease

Kills
FLEAS & Prevents Infestations

Treats and Controls
INTESTINAL WORMS

Adult Hookworm, Roundworm, and Whipworm

For use in dogs and puppies 8 weeks of age
and older and 5 lbs of body weight or greater

STARTS
Killing Fleas
in 30 mins.

MONTHLY
Use

GIVE WITH
A Meal

Elanco™

Principal Display Panel - Trifexis 270 mg Carton Label

Trifexis™

(spinosad + milbemycin oxime)

FOR DOGS
10.1-20 lbs

6
CHEWABLE
TABLETS

270 mg spinosad/
4.5 mg milbemycin oxime

CAUTION: Federal (USA) law restricts this drug to
use by or on the order of a licensed veterinarian.

Prevents
HEARTWORM Disease

Kills
FLEAS & Prevents Infestations

Treats and Controls
INTESTINAL WORMS

Adult Hookworm, Roundworm, and Whipworm

For use in dogs and puppies 8 weeks of age
and older and 5 lbs of body weight or greater

STARTS
Killing Fleas
in 30 mins.

MONTHLY
Use

GIVE WITH
A Meal

Elanco™

Principal Display Panel - Trifexis 560 mg Carton Label

Trifexis™

(spinosad + milbemycin oxime)

FOR DOGS
20.1-40 lbs

6
CHEWABLE
TABLETS

560 mg spinosad/
9.3 mg milbemycin oxime

CAUTION: Federal (USA) law restricts this drug to
use by or on the order of a licensed veterinarian.

Prevents
HEARTWORM Disease

Kills
FLEAS & Prevents Infestations

Treats and Controls
INTESTINAL WORMS

Adult Hookworm, Roundworm, and Whipworm

For use in dogs and puppies 8 weeks of age
and older and 5 lbs of body weight or greater

STARTS
Killing Fleas
in 30 mins.

MONTHLY
Use

GIVE WITH
A Meal

Elanco™

Principal Display Panel - Trifexis 810 mg Carton Label

Trifexis™

(spinosad + milbemycin oxime)

FOR DOGS
40.1-60 lbs

6
CHEWABLE
TABLETS

810 mg spinosad/
13.5 mg milbemycin oxime

CAUTION: Federal (USA) law restricts this drug to
use by or on the order of a licensed veterinarian.

Prevents
HEARTWORM Disease

Kills
FLEAS & Prevents Infestations

Treats and Controls
INTESTINAL WORMS

Adult Hookworm, Roundworm, and Whipworm

For use in dogs and puppies 8 weeks of age
and older and 5 lbs of body weight or greater

STARTS
Killing Fleas
in 30 mins.

MONTHLY
Use

GIVE WITH
A Meal

Elanco™

Principal Display Panel - Trifexis 1620 mg Carton Label

Trifexis™

(spinosad + milbemycin oxime)

FOR DOGS
60.1-120 lbs

6
CHEWABLE
TABLETS

1620 mg spinosad/
27 mg milbemycin oxime

CAUTION: Federal (USA) law restricts this drug to
use by or on the order of a licensed veterinarian.

Prevents
HEARTWORM Disease

Kills
FLEAS & Prevents Infestations

Treats and Controls
INTESTINAL WORMS

Adult Hookworm, Roundworm, and Whipworm

For use in dogs and puppies 8 weeks of age
and older and 5 lbs of body weight or greater

STARTS
Killing Fleas
in 30 mins.

MONTHLY
Use

GIVE WITH
A Meal

Elanco™